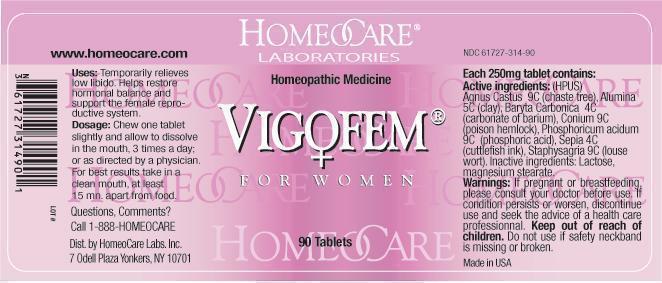 DRUG LABEL: Vigofem for Women
NDC: 61727-314 | Form: TABLET
Manufacturer: Homeocare Laboratories
Category: homeopathic | Type: HUMAN OTC DRUG LABEL
Date: 20210113

ACTIVE INGREDIENTS: CHASTE TREE 9 [hp_C]/90 1; ALUMINUM OXIDE 5 [hp_C]/90 1; BARIUM CARBONATE 4 [hp_C]/90 1; CONIUM MACULATUM FLOWERING TOP 9 [hp_C]/90 1; PHOSPHORIC ACID 9 [hp_C]/90 1; SEPIA OFFICINALIS JUICE 4 [hp_C]/90 1; DELPHINIUM STAPHISAGRIA SEED 9 [hp_C]/90 1
INACTIVE INGREDIENTS: LACTOSE; MAGNESIUM STEARATE

Vigofem for Women

Active ingredients:

Agnus Castus 9C (chaste tree), Alumina 5C (clay), Baryta Carbonica 4C (carbonite of barium), Conium 9C (poison hemlock), Phosphoricum acidum 9C (phosphoric acid), Sepia 4C (cuttlefish ink), Staphysagria 9c (louse wort).

Inactive ingredients:

Lactose, magnesium stearate.

Purpose:

Temporarily relieves low libido. Helps restore hormonal balance and support the female reproductive system.

Keep out of reach of children.

Warnings:

If pregnant or breastfeeding please consult your doctor before use. If condition persists or worsen, discontinue use and seek the advice of a health care professional. Keep out of reach of children. Do not use if safety neckband is missing or broken.

Dosage & Administration:

Chew one tablet slightly and allow to dissolve in the mouth, 3 times a day; or as directed by a physician. For best results take in a clean mouth, at least 15 mn. apart from food.

Indications and Usage:

Chew one tablet slightly and allow to dissolve in the mouth, 3 times a day; or as directed by a physician. For best results take in a clean mouth, at least 15 mn. apart from food.

Vigofem for Women

Homeopathic Medicine

90 Tablets

Vigofem-for-Women.jpg